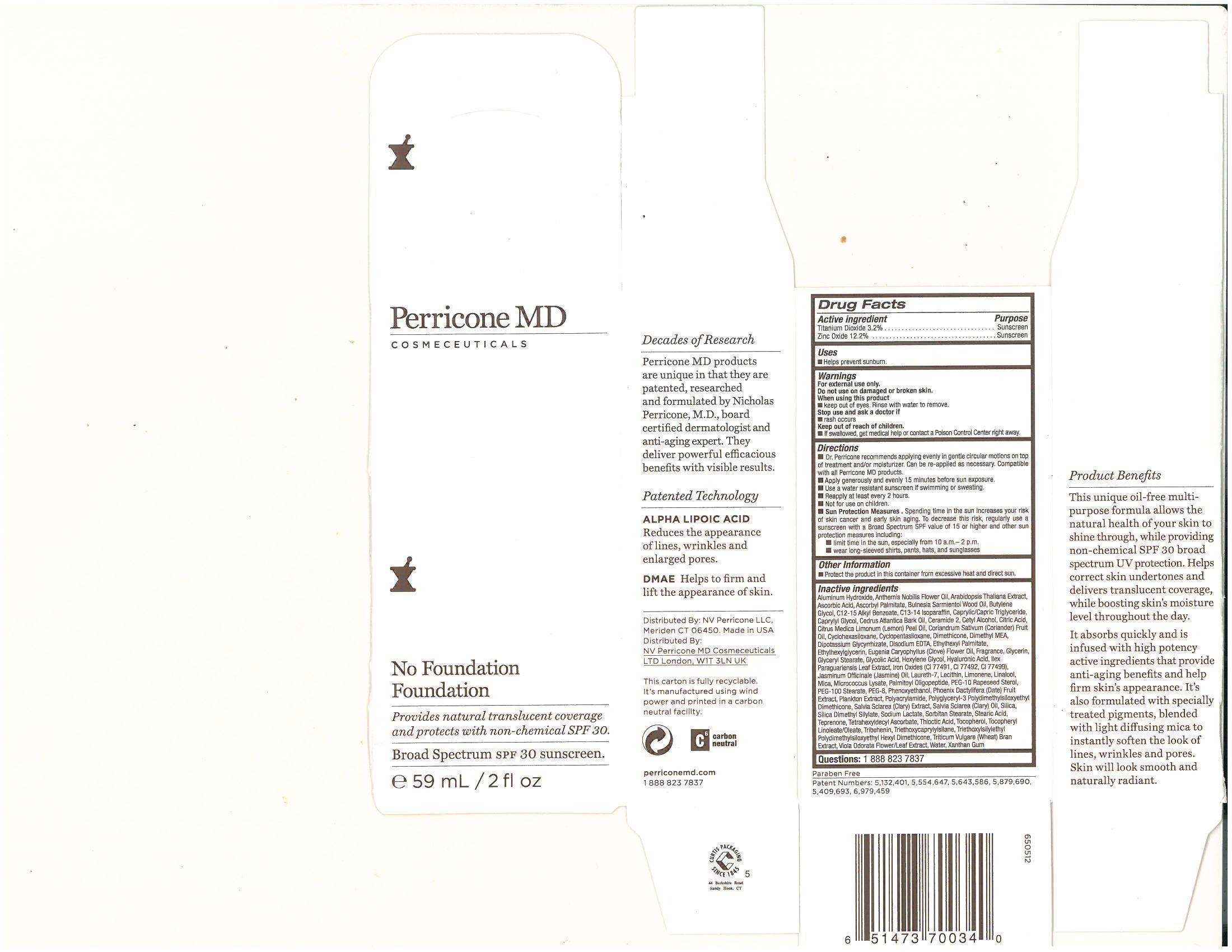 DRUG LABEL: No Foundation SPF 30
                
                
NDC: 62742-4061 | Form: CREAM
Manufacturer: Allure Labs, Inc.
Category: otc | Type: HUMAN OTC DRUG LABEL
Date: 20131231

ACTIVE INGREDIENTS: ZINC OXIDE 122 mg/1 mL; TITANIUM DIOXIDE 32 mg/1 mL
INACTIVE INGREDIENTS: WATER; CYCLOMETHICONE 5; BUTYLENE GLYCOL; GLYCERIN; GLYCERYL MONOSTEARATE; POLYOXYL 100 STEARATE; TETRAHEXYLDECYL ASCORBATE; C12-15 ALKYL BENZOATE; SORBITAN MONOSTEARATE; MEDIUM-CHAIN TRIGLYCERIDES; ETHYLHEXYL PALMITATE; CYCLOMETHICONE 6; FERRIC OXIDE RED; FERRIC OXIDE YELLOW; FERROSOFERRIC OXIDE; GLYCOLIC ACID; 2-(DIETHYLAMINO)ETHANOL; MICA; PHENOXYETHANOL; CITRIC ACID MONOHYDRATE; TRIBEHENIN; CAPRYLYL GLYCOL; LECITHIN, SOYBEAN; CETYL ALCOHOL; ALPHA-TOCOPHEROL, D-; ALPHA LIPOIC ACID; DIMETHICONE; HEXYLENE GLYCOL; ETHYLHEXYLGLYCERIN; XANTHAN GUM; POLYETHYLENE GLYCOL 400; CYCLOMETHICONE; ACRYLAMIDE; LEMON OIL; LIMONENE, (+)-; SODIUM LACTATE; ALUMINUM HYDROXIDE; STEARIC ACID; C13-14 ISOPARAFFIN; EDETATE DISODIUM; GLYCYRRHIZINATE DIPOTASSIUM; ALPHA-TOCOPHEROL; DATE; TEPRENONE; LINALOOL, D-; LAURETH-7; SILICON DIOXIDE; ASCORBYL PALMITATE; HYALURONIC ACID; ASCORBIC ACID; CLARY SAGE; ILEX PARAGUARIENSIS LEAF; GUAIAC OIL; CORIANDER OIL; CLOVE OIL; WHEAT BRAN; CHAMAEMELUM NOBILE FLOWER; JASMINUM OFFICINALE FLOWER; VIOLA ODORATA

Drug Facts

PURPOSE:

Sunscreen

USES:

- Helps prevent sunburn
- Higher SPF gives more sunburn protection

WARNINGS:

- For external use only

WHEN USING THIS PRODUCT:

- Keep out of eyes. Rinse with water to remove.

STOP USE AND ASK A DOCTOR IF

- Rash or irritation develops and lasts.

KEEP OUT OF REACH OF CHILDREN

If swallowed, get medical help or contact a Poison Control Center right away.

DIRECTIONS:

- Dr. Perricone recommends applying evenly in gentle circular motions on top of treatment and or moisturizer. Can be re-applied as necessary. Compatible with all Perricone MD products.
- Not for use on children.

STORAGE:

- Store at room temperature.

OTHER INFORMATION:

- Sun alert: Limiting sun exposure, wearing protective clothing, and using sunscreen may reduce the risk of skin aging, skin cancer, and other harmful effects of the sun.
- Lot No. and exp date: See bottom of carton.

INACTIVE INGREDIENTS:

Aqua (Water), Cyclopentasiloxane, Butylene Glycol, Glycerin, Glyceryl Stearate, PEG-100 Stearate, Tetrahexyldecyl Ascorbate, C12-15 Alkyl Benzoate, Dimethicone, Sorbitan Stearate, Caprylic/Capric Triglyceride, Ethylhexyl Palmitate, Cyclohexasiloxane, Iron Oxides (77499, 77491, 77492), Glycolic Acid, Dimethyl MEA (DMAE), Mica, Phenoxyethanol, Citric Acid, Tribehenin, Caprylyl Glycol, Lecithin, Cetyl Alcohol, Tocopheryl Linoleate/Oleate, Thioctic Acid (Alpha-Lipoic Acid), Polyglyceryl-3 Polydimethylsiloxyethyl Dimethicone, Hexylene Glycol, Ethylhexylglycerin, Xanthan Gum, PEG-8, Triethoxysilylethyl Polydimethylsilxyethyl Hexyl Dimethicone, Polyacrylamide, Citrus Medica Limonum (Lemon) Peel Oil, Limonene, Sodium Lactate, Ceramide-2, Aluminum Hydroxide, Stearic Acid, C13-14 Isoparaffin, PEG-10 Rapeseed Sterol, Disodium EDTA, Dipotassium Glycyrrhizate, Tocopherol, Phoenix Dactylifera (Date) Fruit Extract, Silica Dimethyl Silylate, Teprenone, Triethoxycaprylylsilane, Linalool, Laureth-7, Silica, Ascorbyl Palmitate, Hyaluronic Acid, Ascorbic Acid, Arabidopsis Thaliana Extract, Plankton Extract, Micrococcus Lysate, Palmitoyl Oligopeptide, Salvia Sclarea (Clary) Extract, Cedrus Atlantica Bark Oil, Ilex Paraguariensis Leaf Extract, Bulnesia SarmientoiWood Oil, Coriandrm Sativum (Coriander) Fruit Oil, Salvia Sclarea (Clary) Oil, Eugenia Caryophyllus (Clove) Flower Oil, Triticum Vulgare (Wheat) Bran Extract, Anthemis Nobilis Flower Oil, Jasminum Officinale (Jasmine) Oil, Viola Odorata Flower/Leaf Extract.

PACKAGE LABEL

DISTRIBUTOR (US):

NV Perricone LLC,

Meriden CT 06450.

DISTRIBUTOR (UK):

NV Perricone MD Cosmeceuticals LTD

London, W1T 3LN UK

www.perriconemd.com

1 888 823 7837

IMAGE OF THE PRODUCT: